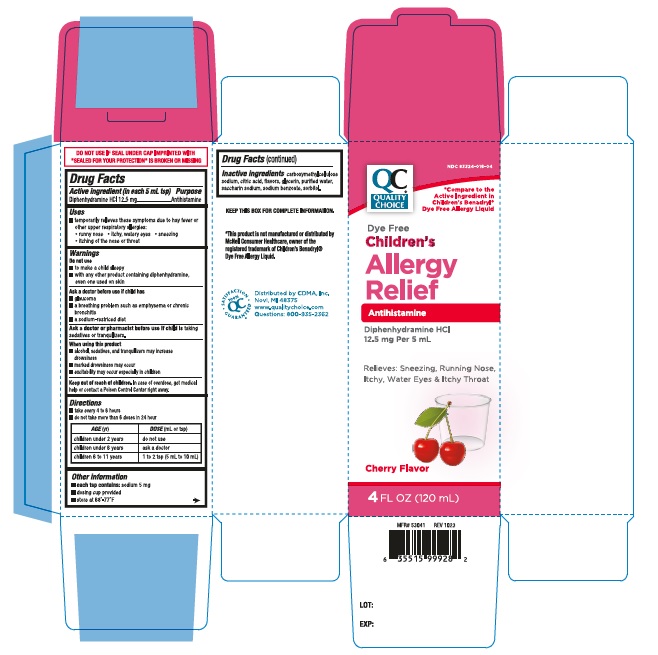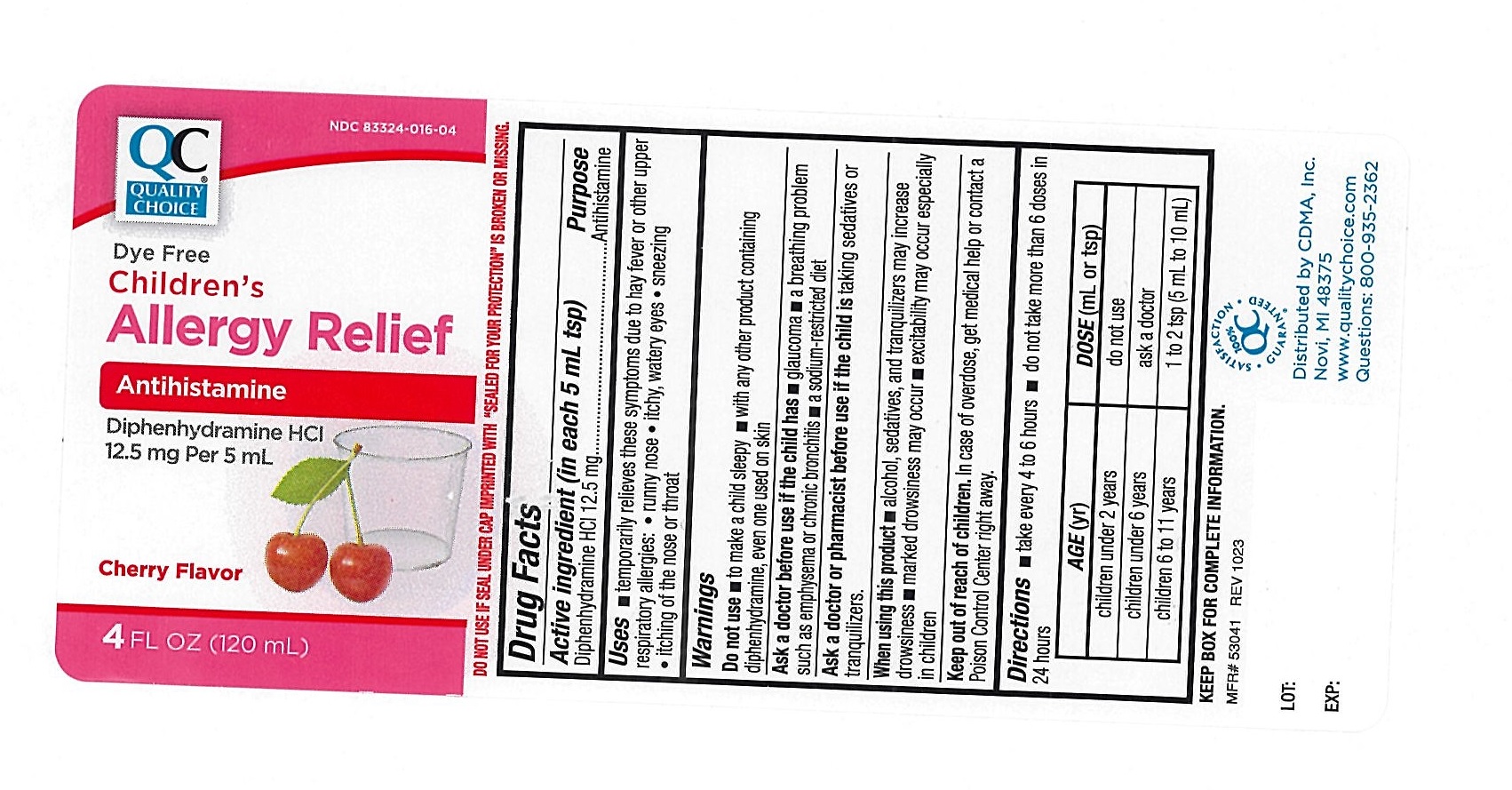 DRUG LABEL: Quality Choice Dye Free Cherry Childrens Allergy Relief
NDC: 83324-016 | Form: LIQUID
Manufacturer: Chain Drug Marketing Association Inc.
Category: otc | Type: Human OTC Drug Label
Date: 20240318

ACTIVE INGREDIENTS: DIPHENHYDRAMINE HYDROCHLORIDE 12.5 mg/5 mL
INACTIVE INGREDIENTS: CARBOXYMETHYLCELLULOSE SODIUM; ANHYDROUS CITRIC ACID; GLYCERIN; SACCHARIN SODIUM; WATER; SODIUM BENZOATE; SORBITOL

Quality Choice Dye Free childrens Allergy Relief 549

ACTIVE INGREDIENT(S)

Diphenhydramine HCl 12.5 mg

PURPOSE

Antihistamine

USE(S)

temporarily relieves these symptoms due to hay fever or other upper respiratory allergies:

- runny nose
- itchy, watery eyes
- sneezing
- itching of the nose or throat

WARNINGS

.

DO NOT USE

- to make a child sleepy
- with any other product containing diphenhydramine, even one used on skin

ASK A DOCTOR BEFORE USE IF CHILD HAS

- glaucoma
- a breathing problem such as emphysema or chronic bronchitis
- a sodium-restricted diet

ASK A DOCTOR OR PHARMACIST BEFORE USE IF THE CHILD IS

taking sedatives or tranquilizers.

WHEN USING THIS PRODUCT

- alcohol, sedatives and tranquilizers may increase drowsiness
- marked drowsiness may occur
- excitability may occur, especially in children

KEEP OUT OF REACH OF CHILDREN.

In case of overdose, get medical help or contact a Poison Control Center right away.

DIRECTIONS

- take every 4 to 6 hours
- do not take more than 6 doses in 24 hours

AGE(yr) | DOSE(mL or tsp)
children under 2 years | do not use
children under 6 years | ask a doctor
children 6 to 11 years | 1 to 2 tsp (5 mL to 10 mL)

OTHER INFORMATION

- each tsp contains: sodium 5 mg
- dosing cup provided
- store at 68°-77°F

INACTIVE INGREDIENTS

carboxymethylcellulose sodium, citric acid, flavors, glycerin, purified water , saccharin sodium, sodium benzoate, sorbitol.

PRINCIPAL DISPLAY PANEL

NDC 83324-016-04

QC® QUALITY CHOICE

*Compare to the Active Ingredient in Children's Benadryl® Dye Free Allergy Liquid

Dye Free Children's Allergy Relief

Antihistamine

Diphenhydramine HCl

12.5 mg/5ml

Relieves: Sneezing, Runny Nose, Itchy, Watery Eyes & Itchy Throat

CHERRY FLAVOR

4FL OZ(120 mL)